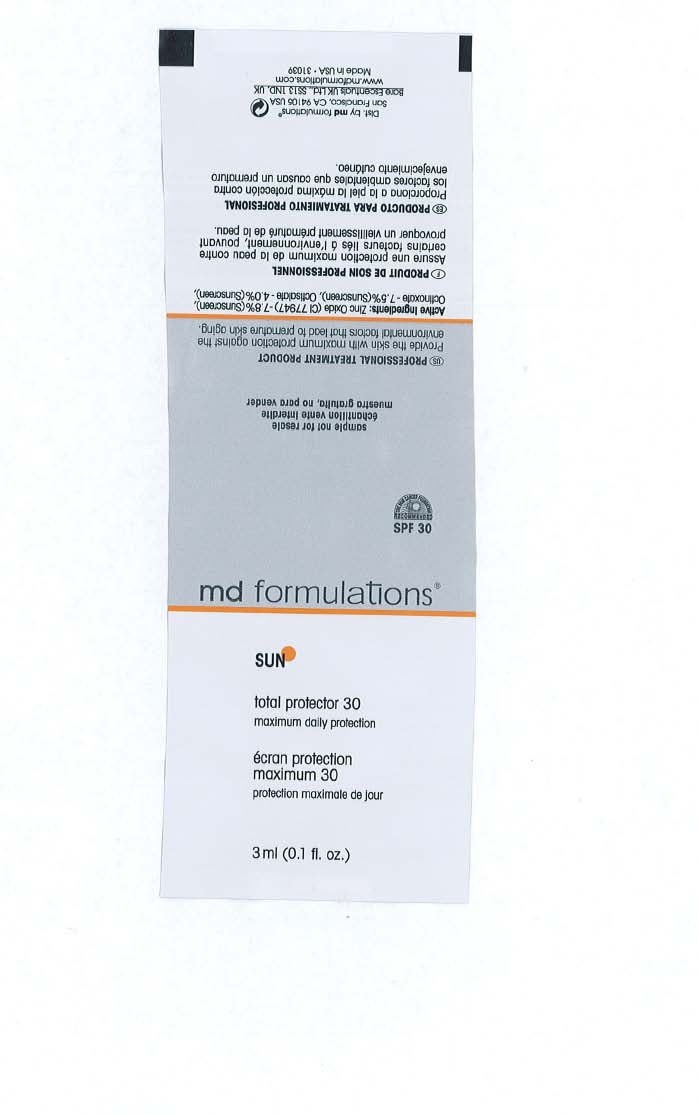 DRUG LABEL: Total Protector 30
NDC: 66078-368 | Form: CREAM
Manufacturer: MD Formulation
Category: otc | Type: HUMAN OTC DRUG LABEL
Date: 20110705

ACTIVE INGREDIENTS: Zinc Oxide 7.8 g/100 g; Octinoxate 7.5 g/100 g; OCTISALATE 4.0 g/100 g
INACTIVE INGREDIENTS: GLYCERIN; ALLANTOIN; EDETATE DISODIUM; XANTHAN GUM; CETYL HYDROXYETHYLCELLULOSE (350000 MW); METHYLPARABEN; Diazolidinyl Urea; Iodopropynyl Butylcarbamate; GLYCERYL MONOSTEARATE; Steareth-2; GLYCERYL MONOSTEARATE; PEG-100 STEARATE; Steareth-100; TRIACONTANYL PVP (WP-660)

Sun Total Protector 30

ACTIVE INGREDIENT

Zinc Oxide - 7.8%
Octinoxate - 7.5%
Octisalate - 4.0%

PURPOSE

Zinc Oxide - 7.8% (Sunscreen)
Octinoxate - 7.5% (Sunscreen)
Octisalate - 4.0% (Sunscreen)

WHEN USING

Provide the skin with maximum protection against the environmental factors that lead to premature skin aging.